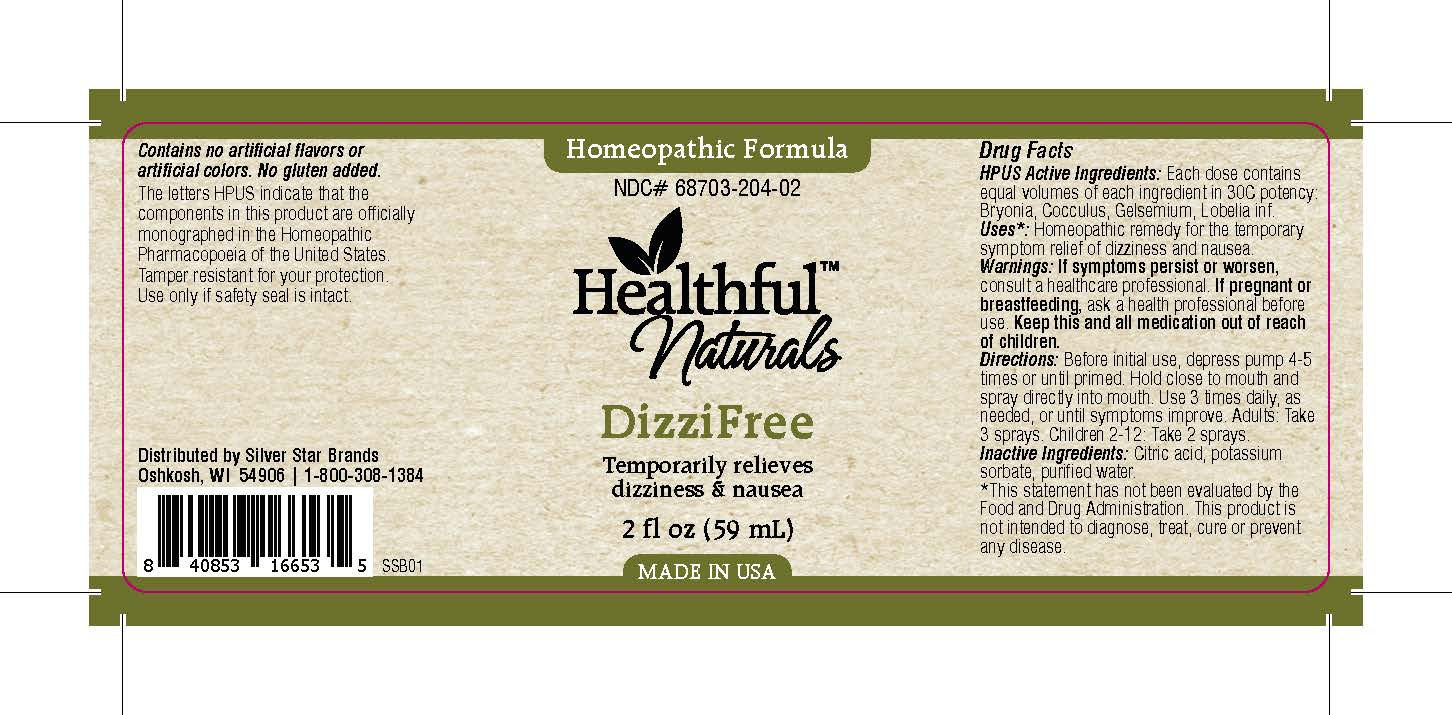 DRUG LABEL: DizziFree
NDC: 68703-204 | Form: SPRAY
Manufacturer: Silver Star Brands
Category: homeopathic | Type: HUMAN OTC DRUG LABEL
Date: 20151110

ACTIVE INGREDIENTS: GELSEMIUM SEMPERVIRENS ROOT 30 [hp_C]/59 mL; BRYONIA ALBA ROOT 30 [hp_C]/59 mL; ANAMIRTA COCCULUS SEED 30 [hp_C]/59 mL; LOBELIA INFLATA 30 [hp_C]/59 mL
INACTIVE INGREDIENTS: ANHYDROUS CITRIC ACID; POTASSIUM SORBATE; WATER

Healthful™ Naturals DizziFree

HPUS Active Ingredients

Each dose contains equal volumes of each ingredient in 30C potency: Bryonia, Cocculus, Gelsemium, Lobelia inf.

Uses

*Homeopathic remedy for the temporary symptom relief of dizziness and nausea. *This statement has not been evaluated by the Food and Drug Administration. This product is not intended to diagnose, treat, cure or prevent any disease.

Warnings

If symptoms persist or worsen, consult a healthcare professional. If pregnant or breastfeeding, ask a health professional before use. Keep this and all medication out of reach of children.

Directions

Before initial use, depress pump 4-5 times or until primed. Hold close to mouth and spray directly into mouth. Use 3 times daily, as needed, or until symptoms improve. Adults: Take 3 sprays. Children 2-12: Take 2 sprays.

Other Information

Contains no artificial flavors or artificial colors. No gluten added. The letters HPUS indicate that the components in this product are officially monographed in the Homeopathic Pharmacopoeia of the United States. Tamper resistant for your protection. Use only if safety seal is intact.

INACTIVE INGREDIENT

Citric acid, potassium sorbate, purified water

KEEP OUT OF REACH OF CHILDREN

Keep this and all medication out of reach of children.

PREGNANCY OR BREAST FEEDING

If pregnant or breastfeeding, ask a health professional before use.

PURPOSE

Temporarily relieves dizziness & nausea